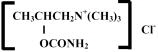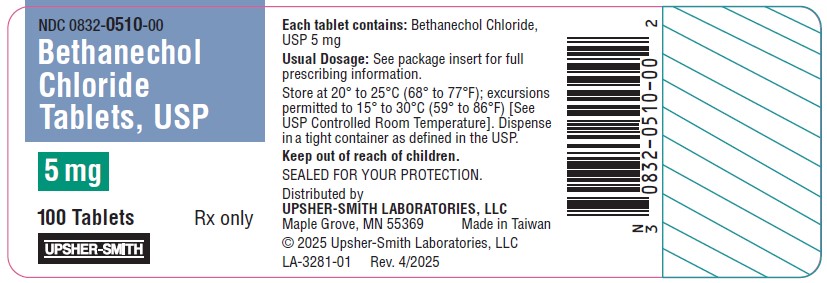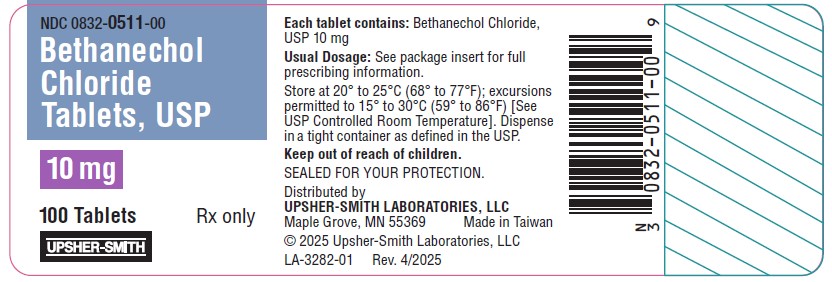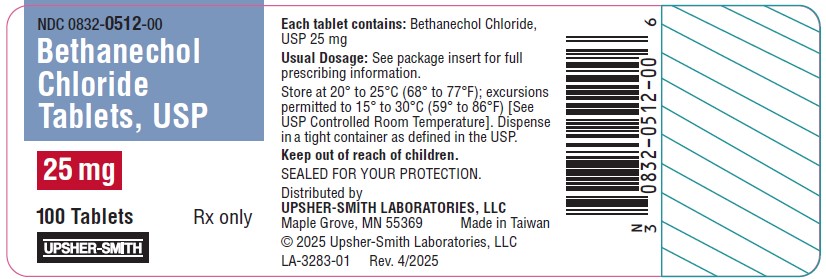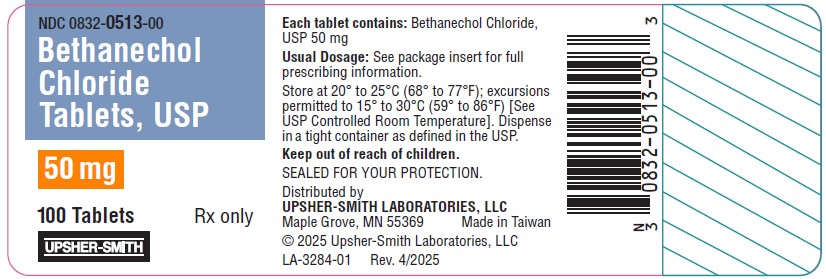 DRUG LABEL: Bethanechol Chloride
NDC: 0832-0510 | Form: TABLET
Manufacturer: Upsher-Smith Laboratories, LLC
Category: prescription | Type: HUMAN PRESCRIPTION DRUG LABEL
Date: 20251216

ACTIVE INGREDIENTS: BETHANECHOL CHLORIDE 5 mg/1 1
INACTIVE INGREDIENTS: SILICON DIOXIDE; LACTOSE MONOHYDRATE; MAGNESIUM STEARATE; MICROCRYSTALLINE CELLULOSE; SODIUM STARCH GLYCOLATE TYPE A POTATO

BETHANECHOL CHLORIDE TABLETS, USP
5 mg, 10 mg, 25 mg and 50 mg

Rx only

DESCRIPTION

Bethanechol chloride, USP, a cholinergic agent, is a synthetic ester which is structurally and pharmacologically related to acetylcholine.

It is designated chemically as 2-[(aminocarbonyl)oxy]- N, N, N-trimethyl-1-propanaminium chloride. Its molecular formula is C7H17ClN2O2and its structural formula is:

It is a white, hygroscopic crystalline powder having a slight amine-like odor, freely soluble in water, and has a molecular weight of 196.68.

Each tablet for oral administration contains 5 mg, 10 mg, 25 mg or 50 mg bethanechol chloride, USP. Tablets also contain the following inactive ingredients: colloidal silicon dioxide, lactose monohydrate, magnesium stearate, microcrystalline cellulose, sodium starch glycolate, (25 mg and 50 mg) D&C Yellow #10 Lake and FD&C Yellow #6 Lake.

CLINICAL PHARMACOLOGY

Bethanechol chloride acts principally by producing the effects of stimulation of the parasympathetic nervous system. It increases the tone of the detrusor urinae muscle, usually producing a contraction sufficiently strong to initiate micturition and empty the bladder. It stimulates gastric motility, increases gastric tone and often restores impaired rhythmic peristalsis.

Stimulation of the parasympathetic nervous system releases acetylcholine at the nerve endings. When spontaneous stimulation is reduced and therapeutic intervention is required, acetylcholine can be given, but it is rapidly hydrolyzed by cholinesterase and its effects are transient. Bethanechol chloride is not destroyed by cholinesterase and its effects are more prolonged than those of acetylcholine.

Effects on the GI and urinary tracts sometimes appear within 30 minutes after oral administration of bethanechol chloride, but more often 60 to 90 minutes are required to reach maximum effectiveness. Following oral administration, the usual duration of action of bethanechol chloride is one hour, although large doses (300 to 400 mg) have been reported to produce effects for up to six hours. Subcutaneous injection produces a more intense action on bladder muscle than does oral administration of the drug.

Because of the selective action of bethanechol chloride, nicotinic symptoms of cholinergic stimulation are usually absent or minimal when orally or subcutaneously administered in therapeutic doses, while muscarinic effects are prominent. Muscarinic effects usually occur within 5 to 15 minutes after subcutaneous injection, reach a maximum in 15 to 30 minutes, and disappear within two hours. Doses that stimulate micturition and defecation and increase peristalsis do not ordinarily stimulate ganglia or voluntary muscles. Therapeutic test doses in normal human subjects have little effect on heart rate, blood pressure or peripheral circulation.

Bethanechol chloride does not cross the blood-brain barrier because of its charged quaternary amine moiety. The metabolic rate and mode of excretion of the drug have not been elucidated.

A clinical study (Diokno, A.C.; Lapides, J.; Urol 10: 23-24, July 1977) was conducted on the relative effectiveness of oral and subcutaneous doses of bethanechol chloride on the stretch response of bladder muscle in patients with urinary retention. Results showed that 5 mg of the drug given subcutaneously stimulated a response that was more rapid in onset and of larger magnitude than an oral dose of 50 mg, 100 mg, or 200 mg. All the oral doses, however, had a longer duration of effect than the subcutaneous dose. Although the 50 mg oral dose caused little change in intravesical pressure in this study, this dose has been found in other studies to be clinically effective in the rehabilitation of patients with decompensated bladders.

INDICATIONS AND USAGE

Bethanechol chloride tablets are indicated for the treatment of acute postoperative and postpartum nonobstructive (functional) urinary retention and for neurogenic atony of the urinary bladder with retention.

CONTRAINDICATIONS

Hypersensitivity to bethanechol chloride tablets, hyperthyroidism, peptic ulcer, latent or active bronchial asthma, pronounced bradycardia or hypotension, vasomotor instability, coronary artery disease, epilepsy and parkinsonism.

Bethanechol chloride should not be employed when the strength or integrity of the gastrointestinal or bladder wall is in question, or in the presence of mechanical obstruction; when increased muscular activity of the gastrointestinal tract or urinary bladder might prove harmful, as following recent urinary bladder surgery, gastrointestinal resection and anastomosis, or when there is possible gastrointestinal obstruction; in bladder neck obstruction, spastic gastrointestinal disturbances, acute inflammatory lesions of the gastrointestinal tract, or peritonitis; or in marked vagotonia.

PRECAUTIONS

General

In urinary retention, if the sphincter fails to relax as bethanechol chloride contracts the bladder, urine may be forced up the ureter into the kidney pelvis. If there is bacteriuria, this may cause reflux infection.

Information for Patients

Bethanechol chloride tablets should preferably be taken one hour before or two hours after meals to avoid nausea or vomiting. Dizziness, lightheadedness or fainting may occur, especially when getting up from a lying or sitting position.

Drug Interactions

Special care is required if this drug is given to patients receiving ganglion blocking compounds because a critical fall in blood pressure may occur. Usually, severe abdominal symptoms appear before there is such a fall in the blood pressure.

Carcinogenesis, Mutagenesis, Impairment of Fertility

Long-term studies in animals have not been performed to evaluate the effects upon fertility, mutagenic or carcinogenic potential of bethanechol chloride.

Pregnancy

Teratogenic Effects

Animal reproduction studies have not been conducted with bethanechol chloride. It is also not known whether bethanechol chloride can cause fetal harm when administered to a pregnant woman or can affect reproduction capacity. Bethanechol chloride should be given to a pregnant woman only if clearly needed.

Nursing Mothers

It is not known whether this drug is secreted in human milk. Because many drugs are secreted in human milk and because of the potential for serious adverse reactions from bethanechol chloride in nursing infants, a decision should be made whether to discontinue nursing or to discontinue the drug, taking into account the importance of the drug to the mother.

Pediatric Use

Safety and effectiveness in pediatric patients have not been established.

ADVERSE REACTIONS

Adverse reactions are rare following oral administration of bethanechol chloride, but are more common following subcutaneous injection. Adverse reactions are more likely to occur when dosage is increased.

The following adverse reactions have been observed: Body as a Whole: malaise; Digestive: abdominal cramps or discomfort, colicky pain, nausea and belching, diarrhea, borborygmi, salivation; Renal: urinary urgency; Nervous System: headache; Cardiovascular: a fall in blood pressure with reflex tachycardia, vasomotor response; Skin: flushing producing a feeling of warmth, sensation of heat about the face, sweating; Respiratory: bronchial constriction, asthmatic attacks; Special Senses: lacrimation, miosis.

Causal Relationship Unknown

The following adverse reactions have been reported, and a causal relationship to therapy with bethanechol chloride has not been established: Body as a Whole: malaise; Nervous System: seizures.

OVERDOSAGE

Early signs of overdosage are abdominal discomfort, salivation, flushing of the skin ("hot feeling"), sweating, nausea, and vomiting.

Atropine Sulfate is a specific antidote. The recommended dose for adults is 0.6 mg. Repeat doses can be given every two hours, according to clinical response. The recommended dosage in infants and children up to 12 years of age is 0.01 mg/kg (to a maximum single dose of 0.4 mg) repeated every two hours as needed until the desired effect is obtained or adverse effects of atropine preclude further usage. Subcutaneous injection of atropine is preferred except in emergencies when the intravenous route may be employed.

The oral LD50of bethanechol chloride is 1510 mg/kg in the mouse.

DOSAGE AND ADMINISTRATION

Dosage must be individualized, depending on the type and severity of the condition to be treated.

Preferably give the drug when the stomach is empty. If taken soon after eating, nausea and vomiting may occur.

The usual adult oral dose ranges from 10 to 50 mg three or four times a day. The minimum effective dose is determined by giving 5 to 10 mg initially and repeating the same amount at hourly intervals until satisfactory response occurs, or until a maximum of 50 mg has been given. The effects of the drug sometimes appear within 30 minutes and are usually maximal within 60 to 90 minutes. The drug effects persist for about one hour.

If necessary, the effects of the drug can be abolished promptly by atropine [see OVERDOSAGE] .

HOW SUPPLIED

Bethanechol Chloride Tablets, USP

5 mg tablets are white, 7/16" diameter, round flat faced bevel edge tablets; one side scored and debossed BCL bisect 5, one side debossed 832. They are supplied as follows:

Bottles of 100 tablets | NDC 0832-0510-00
Unit-dose cartons of 100 tablets | NDC 0832-0510-01

10 mg tablets are white, 7/16" diameter, round flat faced bevel edge tablets; one side scored and debossed BCL bisect 10, one side debossed 832. They are supplied as follows:

Bottles of 100 tablets | NDC 0832-0511-00
Unit-dose cartons of 100 tablets | NDC 0832-0511-01

25 mg tablets are yellow, 7/16" diameter, round flat faced bevel edge tablets; one side scored and debossed BCL bisect 25, one side debossed 832. They are supplied as follows:

Bottles of 100 tablets | NDC 0832-0512-00
Unit-dose cartons of 100 tablets | NDC 0832-0512-01

50 mg tablets are yellow, 7/16" diameter, round flat faced bevel edge tablets; one side scored and debossed BCL bisect 50, one side debossed 832. They are supplied as follows:

Bottles of 100 tablets | NDC 0832-0513-00
Unit-dose cartons of 100 tablets | NDC 0832-0513-01

STORAGE AND HANDLING

Store at 20° to 25°C (68° to 77°F); excursions permitted to 15° to 30°C (59° to 86°F) [See USP Controlled Room Temperature].

Dispense in a tight container as defined in the USP.

Keep out of reach of children.

Distributed by
UPSHER-SMITH LABORATORIES, LLC
Maple Grove, MN 55369

Made in Taiwan

Revised: 4/2025

PRINCIPAL DISPLAY PANEL - 10 mg Tablet Bottle Label

NDC 0832-0511-00

Bethanechol
Chloride
Tablets, USP

10 mg

100 Tablets
Rx only

UPSHER-SMITH

PRINCIPAL DISPLAY PANEL - 5 mg Tablet Bottle Label

NDC 0832-0510-00

Bethanechol
Chloride
Tablets, USP

5 mg

100 Tablets
Rx only

UPSHER-SMITH

PRINCIPAL DISPLAY PANEL - 25 mg Tablet Bottle Label

NDC 0832-0512-00

Bethanechol
Chloride
Tablets, USP

25 mg

100 Tablets
Rx only

UPSHER-SMITH

PRINCIPAL DISPLAY PANEL - 50 mg Tablet Bottle Label

NDC 0832-0513-00

Bethanechol
Chloride
Tablets, USP

50 mg

100 Tablets
Rx only

UPSHER-SMITH